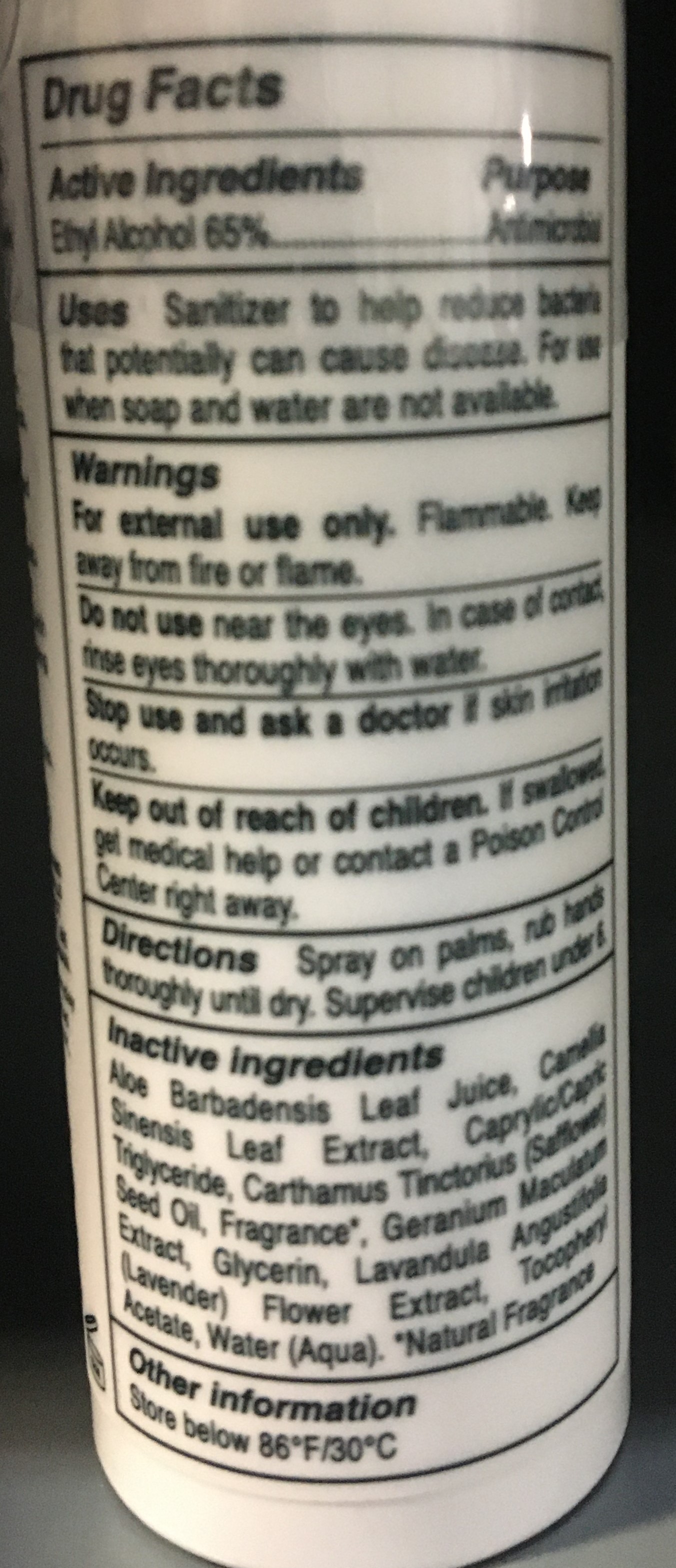 DRUG LABEL: Germaphobe Crisp Pine Hand Sanitizer
NDC: 72496-1115 | Form: SPRAY
Manufacturer: Naturich Labs
Category: otc | Type: HUMAN OTC DRUG LABEL
Date: 20230412

ACTIVE INGREDIENTS: ALCOHOL 65 mL/100 mL
INACTIVE INGREDIENTS: WATER 65 mL/100 mL

EGL Germaphobe Crisp Pine Hand Sanitizer

Active Ingredients

Alcohol 65% v/v. Purpose: Antiseptic

Purpose

Antiseptic, Hand Sanitizer

Use

Hand Sanitizer to help reduce bacteria that potentially can cause disease. For use when soap and water are not available.

Warnings

For external use only. Flammable. Keep away from heat or flame.

Do not use

In children less than 2 months of age
On open skin wounds

When using this product keep out of eyes, ears, and mouth. In case of contact with eyes, rinse eyes thoroughly with water. Stop use and ask doctor if irritation or rash occurs. These may be signs of a serious condition. Keep out of reach of children. If swallowed, get medical help or contact Poison Control Center right away.

Stop use and ask doctor if irritation or rash occurs. These may be signs of a serious condition.

Keep out of reach of children. If swallowed, get medical help or contact a Poison Control Center right away.

Directions

Place enough product on hands to cover all surfaces. Rub hands together until dry.
Supervise children under 6 years of age when using product to avoid swallowing.

Other Information

Store between 15-30C (59-86F)
Avoid freezing and excessive heat above 40C (104F)

Inactive ingredients

Aloe Barbadensis Leaf Juice, Camellia Sinensis Leaf Extract, Caprylic/Capric Triglyceride, Carthamus Tinctorius (Safflower) Seed Oil, Fragrance, Geranium Maculatum Extract, Glycerin, Lavandula Angustifolia (Lavender) Flower Extract, Tocopheryl Acetate, Water (Aqua).